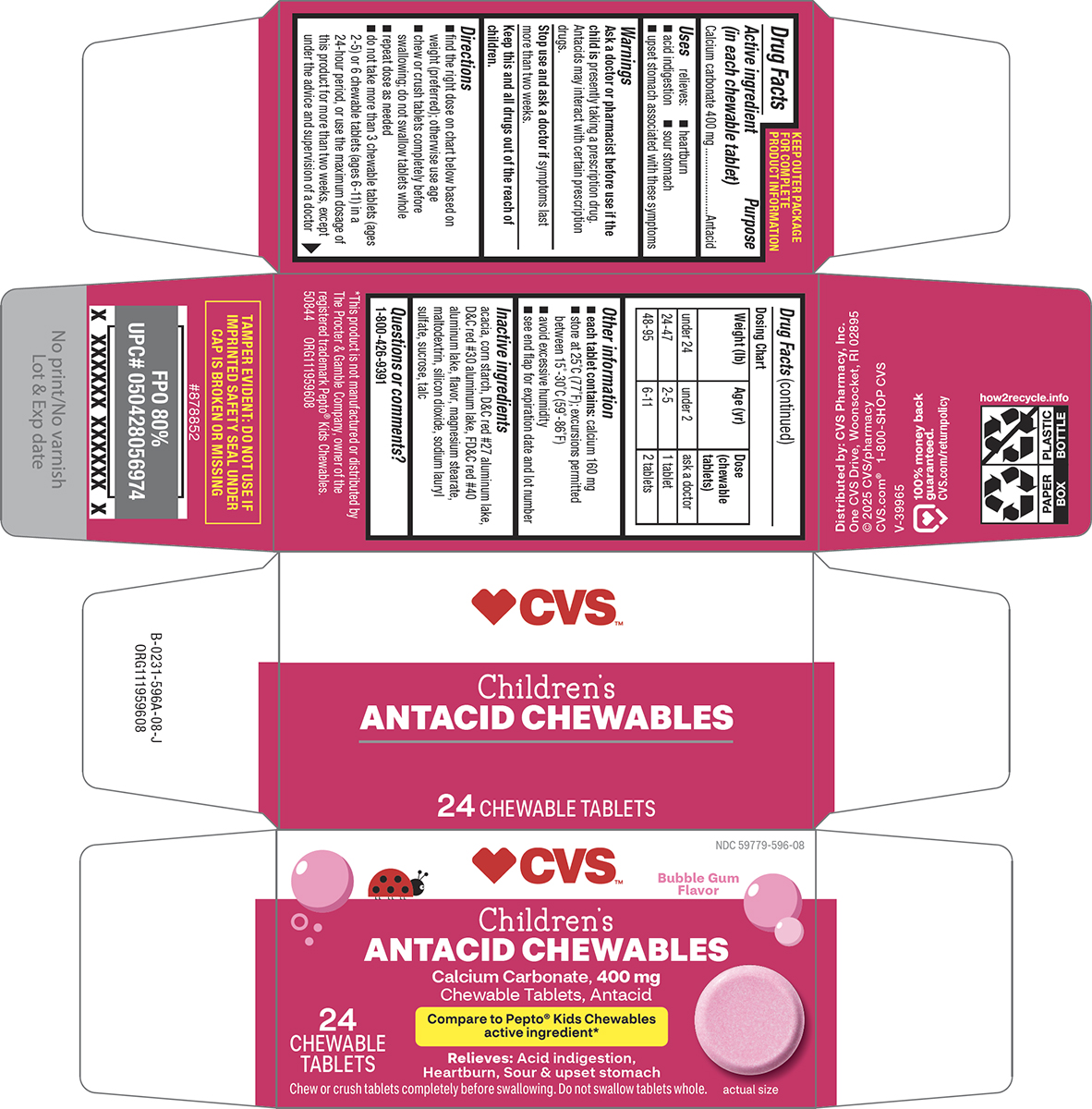 DRUG LABEL: Antacid
NDC: 59779-596 | Form: TABLET, CHEWABLE
Manufacturer: CVS Pharmacy
Category: otc | Type: HUMAN OTC DRUG LABEL
Date: 20251115

ACTIVE INGREDIENTS: CALCIUM CARBONATE 400 mg/1 1
INACTIVE INGREDIENTS: ACACIA; STARCH, CORN; D&C RED NO. 27 ALUMINUM LAKE; D&C RED NO. 30 ALUMINUM LAKE; FD&C RED NO. 40 ALUMINUM LAKE; MAGNESIUM STEARATE; MALTODEXTRIN; SILICON DIOXIDE; SODIUM LAURYL SULFATE; SUCROSE; TALC

CVS 44-596A

Active ingredient (in each chewable tablet)

Calcium carbonate 400 mg

Purpose

Antacid

Uses

relieves:

- heartburn
- acid indigestion
- sour stomach
- upset stomach associated with these symptoms

Warnings

Ask a doctor or pharmacist before use if the child is

presently taking a prescription drug. Antacids may interact with certain prescription drugs.

Stop use and ask a doctor if

symptoms last more than two weeks.

Directions

- find the right dose on chart below based on weight (preferred); otherwise use age
- chew or crush tablets completely before swallowing; do not swallow tablets whole
- repeat dose as needed
- do not take more than 3 chewable tablets (ages 2-5) or 6 chewable tablets (ages 6-11) in a 24-hour period, or use the maximum dosage of this product for more than two weeks, except under the advice and supervision of a doctor

Dosing Chart

Weight (lb) | Age (yr) | Dose (chewable tablets)
under 24 | under 2 | ask a doctor
24-47 | 2-5 | 1 tablet
48-95 | 6-11 | 2 tablets

Other information

- each tablet contains: calcium 160 mg
- store at 25°C (77°F); excursions permitted between 15°-30°C (59°-86°F)
- avoid excessive humidity
- see end flap for expiration date and lot number

Inactive ingredients

acacia, corn starch, D&C red #27 aluminum lake, D&C red #30 aluminum lake, FD&C red #40 aluminum lake, flavor, magnesium stearate, maltodextrin, silicon dioxide, sodium lauryl sulfate, sucrose, talc

Questions or comments?

1-800-426-9391

Principal Display Panel

♥CVS™

NDC 59779-596-08

Bubble Gum
Flavor

Children’s
ANTACID CHEWABLES
Calcium Carbonate, 400 mg
Chewable Tablets, Antacid

Compare to Pepto® Kids Chewables
active ingredient*

Relieves: Acid indigestion,
Heartburn, Sour & upset stomach

24
CHEWABLE
TABLETS

Chew or crush tablets completely before swallowing. Do not swallow tablets whole.

actual size

TAMPER EVIDENT: DO NOT USE IF
IMPRINTED SAFETY SEAL UNDER
CAP IS BROKEN OR MISSING

*This product is not manufactured or distributed by
The Procter & Gamble Company, owner of the
registered trademark Pepto® Kids Chewables.
50844 ORG111959608

Distributed by: CVS Pharmacy, Inc.
One CVS Drive, Woonsocket, RI 02895
© 2025 CVS/pharmacy
CVS.com® 1-800-SHOP CVS

V-39965

100% money back
guaranteed.
CVS.com/returnpolicy

CVS 44-596A